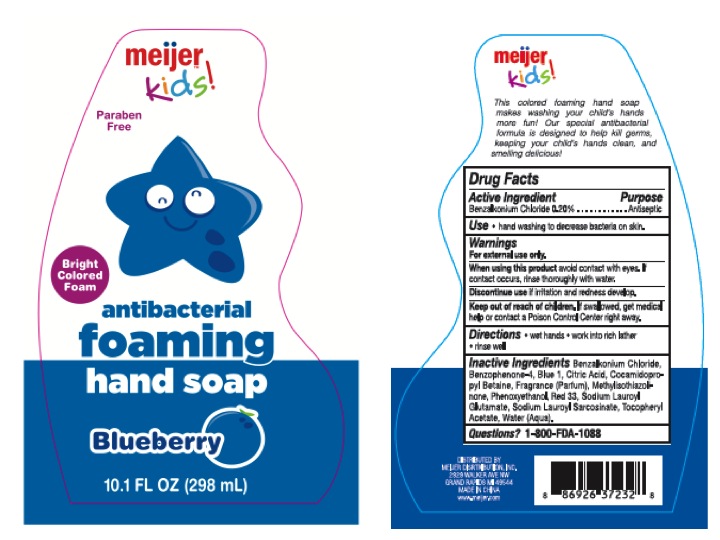 DRUG LABEL: meijer kids
                
NDC: 40104-001 | Form: LOTION
Manufacturer: Ningbo Pulisi Daily Chemical Products Co.,Ltd.
Category: otc | Type: HUMAN OTC DRUG LABEL
Date: 20130922

ACTIVE INGREDIENTS: BENZALKONIUM CHLORIDE .596 g/298 g
INACTIVE INGREDIENTS: BENZOPHENONE; CITRIC ACID MONOHYDRATE; COCAMIDOPROPYL BETAINE; METHYLISOTHIAZOLINONE; PHENOXYETHANOL; D&C RED NO. 33; FD&C RED NO. 40; SODIUM LAUROYL GLUTAMATE; SODIUM LAUROYL SARCOSINATE; .ALPHA.-TOCOPHEROL ACETATE; WATER

Drug Facts

Inactive Ingredients - Benzophenone - 4, Citric Acid, Cocamidopropyl

Betaine, Frangrance (Parfum), Methylisothiazolinone, Phenoxyethanol, Red 33,

Red 40, Sodium Lauroyle Glutamate, Sodium Lauroyle Sarcosinate,

Tocopheryl Acetate, Water (Agua).

Active Ingredient

Benzalkonium Chloride 0.20 %

Purpose

Antiseptic

INDICATIONS AND USAGE

Use - hand washing to decrease bacteria on skin

Warnings

For external use only

When using this product avoid contact with eyes. If

contact occurs, rinse thoroughly with water.

Discontinue use if irritation and redness develop.

Keep out of reach of children. If swallowed, get medical

help or contact a Poison Control Center right away.

DOSAGE AND ADMINISTRATION

Directions - wet hands -- work into rich later

--rinse well

Questions? 1 - 800 - FDA - 1088